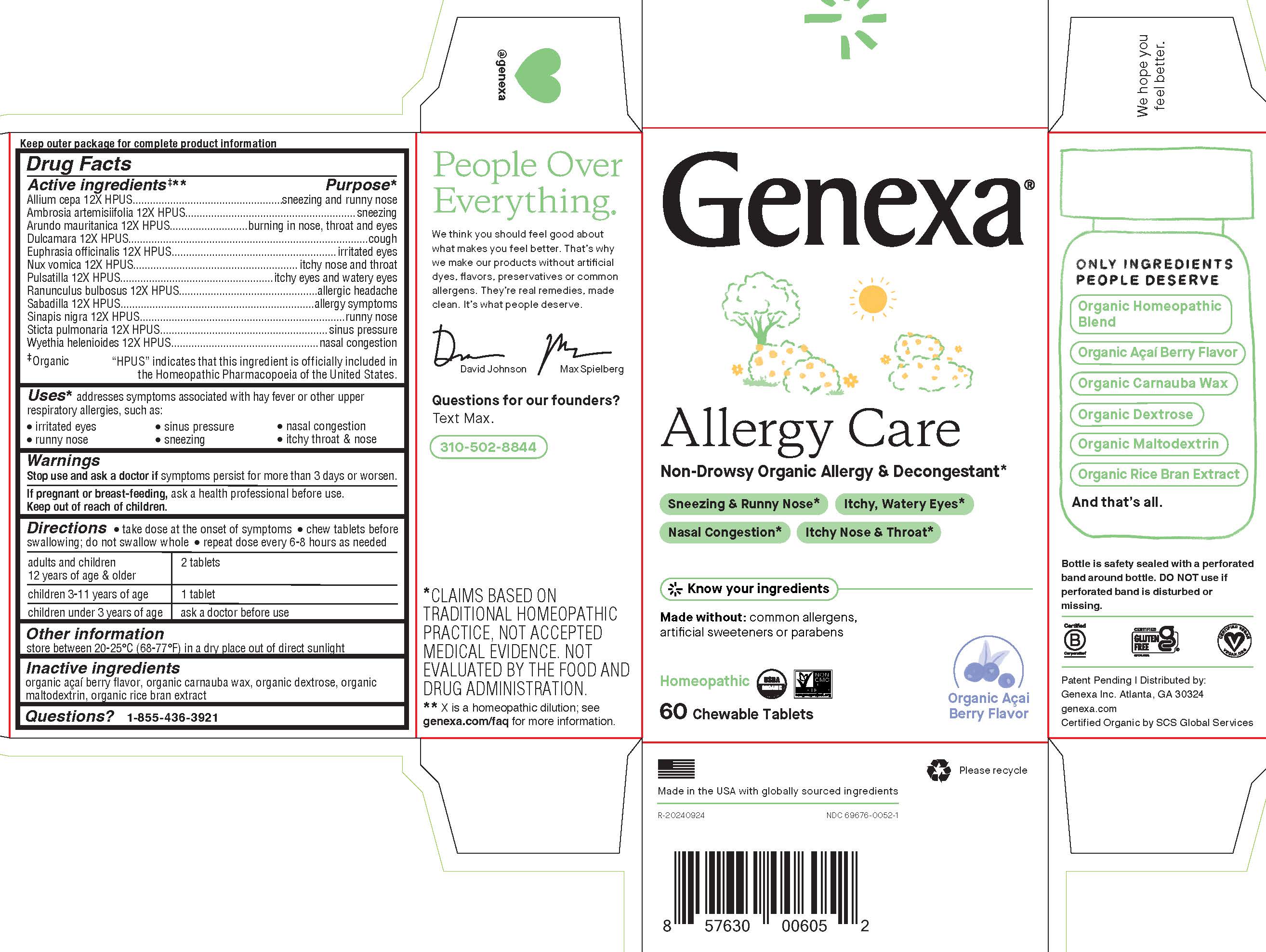 DRUG LABEL: Genexa Allergy Care
NDC: 69676-0052 | Form: TABLET, CHEWABLE
Manufacturer: Genexa Inc.
Category: homeopathic | Type: HUMAN OTC DRUG LABEL
Date: 20250403

ACTIVE INGREDIENTS: AMBROSIA ARTEMISIIFOLIA 12 [hp_X]/1 1; STRYCHNOS NUX-VOMICA SEED 12 [hp_X]/1 1; BLACK MUSTARD SEED 12 [hp_X]/1 1; LOBARIA PULMONARIA 12 [hp_X]/1 1; ARUNDO PLINIANA ROOT 12 [hp_X]/1 1; RANUNCULUS BULBOSUS WHOLE 12 [hp_X]/1 1; PULSATILLA PRATENSIS 12 [hp_X]/1 1; SCHOENOCAULON OFFICINALE SEED 12 [hp_X]/1 1; SOLANUM DULCAMARA TOP 12 [hp_X]/1 1; EUPHRASIA STRICTA 12 [hp_X]/1 1; WYETHIA HELENIOIDES ROOT 12 [hp_X]/1 1; ALLIUM CEPA WHOLE 12 [hp_X]/1 1
INACTIVE INGREDIENTS: RICE BRAN; DEXTROSE; CARNAUBA WAX; MALTODEXTRIN

ALLERGY CARE

Drug Facts

Active ingredients‡**

Allium cepa 12X HPUS

Ambrosia artemisiifolia 12X HPUS

Arundo mauritanica 12X HPUS

Dulcamara 12X HPUS

Euphrasia officinalis 12X HPUS

Nux vomica 12X HPUS

Pulsatilla 12X HPUS

Ranunculus bulbosus 12X HPUS

Sabadilla 12X HPUS

Sinapis nigra 12X HPUS

Sticta pulmonaria 12X HPUS

Wyethia helenioides 12X HPUS

‡ Organic

"HPUS" indicates that this ingredient is officially included in the Homeopathic Pharmacopoeia of the United States.

Purpose*

sneezing and runny nose

sneezing

burning in nose, throat and eyes

cough

irritated eyes

itchy nose and throat

itchy eyes and watery eyes

allergic headache

allergy symptoms

runny nose

sinus pressure

nasal congestion

Uses*

addresses symptoms associated with hay fever or other upper respiratory allergies, such as:

- irritated eyes
- sinus pressure
- nasal congestion
- runny nose
- sneezing
- itchy throat & nose

Warnings

Stop use and ask a doctorifsymptoms persist for more than 3 days or worsen.

PREGNANCY OR BREAST FEEDING

If pregnant or breast-feeding, ask a health professional before use.

Keep out of reach of children.

Directions

- take does at the onset of symptoms
- chew tablets before swallowing; do not swallow whole
- repeat dose every 6-8 hours as needed

adults and children 12 years of age; and older | 2 tablets
children 3-11 years of age | 1 tablet
children under 3 years of age | ask a doctor before use

Other information

store between 20-25° C (68-77° F) in a dry place out of direct sunlight

Inactive ingredients

organic açaí berry flavor, organic carnauba wax, organic dextrose, organic maltodextrin, organic rice bran extract

Questions?

1-855-436-3921

* CLAIMS BASED ON TRADITIONAL HOMEOPATHIC PRACTICE, NOT ACCEPTED MEDICAL EVIDENCE. NOT EVALUATED BY THE FOOD AND DRUG ADMINISTRATION.

** X is a homeopathic dilution; see genexa.com/faq for more information.

Bottle is safety sealed with a perforated band around bottle. DO NOT use if perforated band is disturbed or missing.

Patent Pending | Distributed by:

Genexa Inc. Atlanta, GA 30324

genexa.com

Certified Organic by SCS Global Services

Made in the USA with globally sourced ingredients

NDC 69676-0052-1

PACKAGE LABEL

Genexa®

Allergy Care

Non-Drowsy Organic Allergy & Decongestant*

Sneezing & Runny Nose*

Itchy, Watery Eyes*

Nasal Congestion*

Itchy Nose & Throat*

Know your ingredients

Made without: common allergens, artificial sweeteners or parabens

Homeopathic

60 Chewable Tablets

Organic Açai Berry Flavor